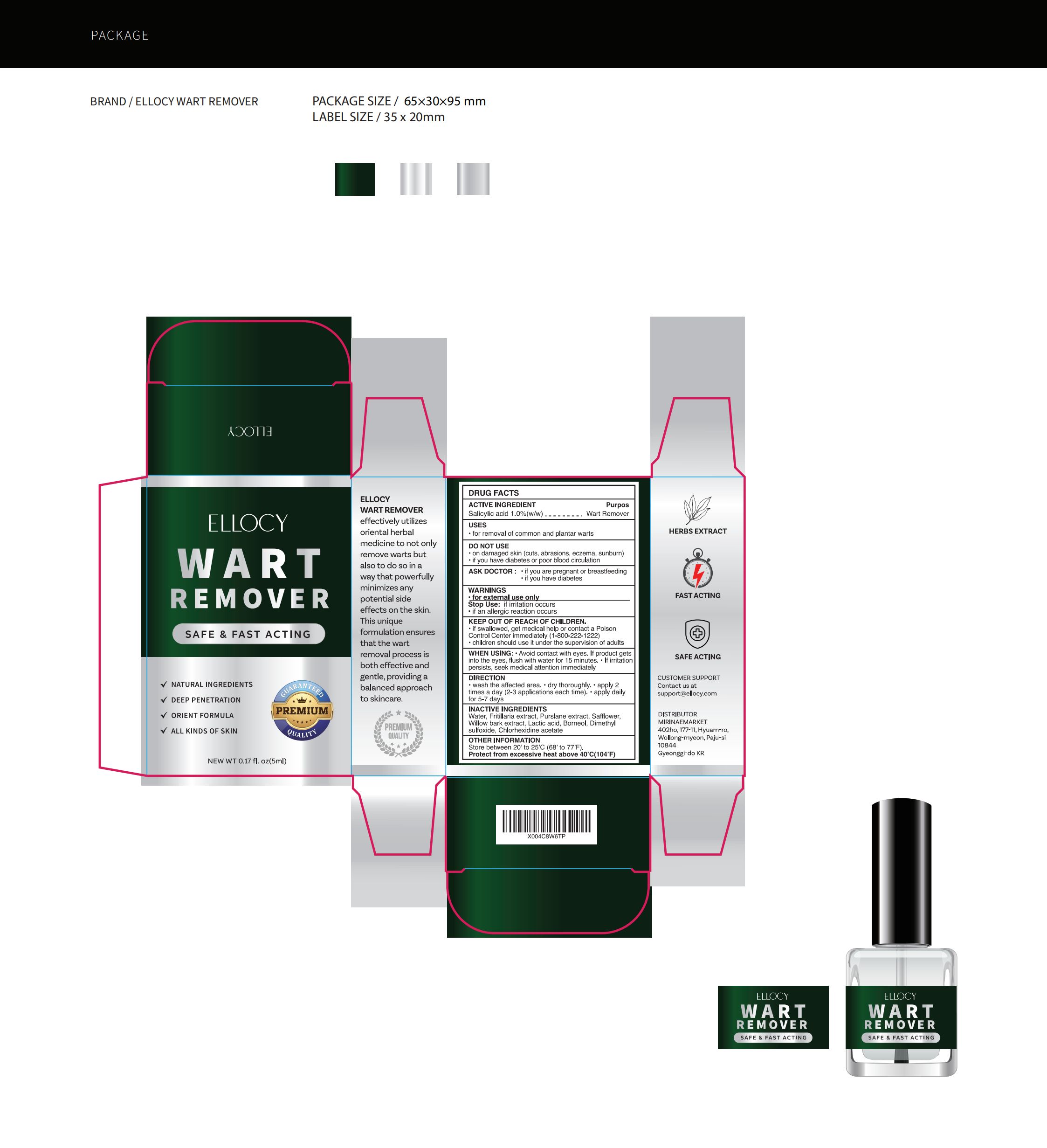 DRUG LABEL: Ellocy Wart remover
NDC: 83596-004 | Form: LIQUID
Manufacturer: Aramode
Category: otc | Type: HUMAN OTC DRUG LABEL
Date: 20240902

ACTIVE INGREDIENTS: SALICYLIC ACID 1 g/100 mL
INACTIVE INGREDIENTS: WILLOW BARK; FRITILLARIA DELAVAYI BULB; SAFFLOWER; DIMETHYL SULFOXIDE; PURSLANE; BORNEOL; WATER; LACTIC ACID; CHLORHEXIDINE ACETATE

83596-004

Active Ingredient

Salicylic acid 1%

Purpose

remove wart

Use

• for removal of common and plantar warts
• the plantar wart is recognized by its location only on the bottom of the foot, its tenderness, and the interruption of the footprint pattern

Warnings

For external use only

Do not use

• On damaged skin (cuts, abrasions, eczema, sunburn).
• If you are pregnant or breastfeeding

When Using

• Aviod contact with eyes.If product gets into the eyes, flush with water for 15 minutes.• If irritation persists, seek medical attention immediately.

Stop Use

if irritation occurs
if an allergic reaction occurs

Ask Doctor

if you are pregnant or breastfeeding
if you have diabetes

Keep Oot Of Reach Of Children

Keep Out Of Reach Of Children

Directions

• wash the affected area.
• dry thoroughly
• apply 2 times a day (2-3 applications each time).
• continue application for 5-7 days.

Other information

Store between 20 to 25℃ (68 to 77F)
Protect from excessive heat above 40℃ (104F)

Inactive ingredients

Fritillaria extract, Purslane extract, Safflower, Willow bark extract, Lactic acid, Borneol, Dimethyl sulfoxide, Chlorhexidine acetate

Questions

CUSTOMER SUPPORT Contact us at support@ellocy.com